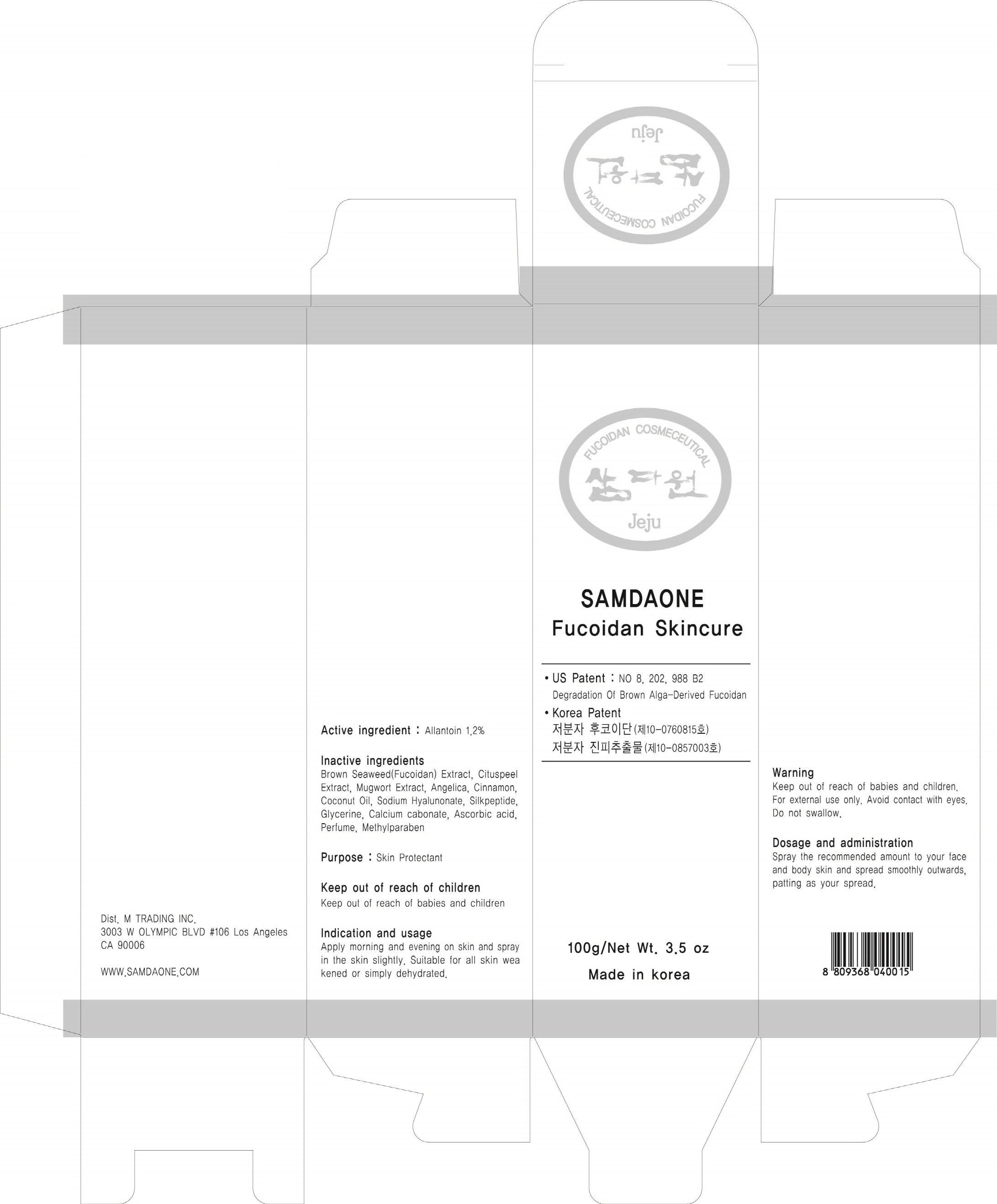 DRUG LABEL: FUCOIDAN SKINCURE
NDC: 58986-010 | Form: SPRAY
Manufacturer: SAMDAONE
Category: otc | Type: HUMAN OTC DRUG LABEL
Date: 20130822

ACTIVE INGREDIENTS: Allantoin 1.2 g/100 g
INACTIVE INGREDIENTS: Glycerin; Methylparaben

ACTIVE INGREDIENT

Active ingredient: Allantoin 1.2%

INACTIVE INGREDIENT

Inactive ingredients:
Brown Seaweed(Fucoidan) Extrect, Cituspeel Extract, Mugwort Extract, Angelica, Cinnamon, Ascorbic acid, Coconut Oil, Sodium Hyalunonate, Silkpeptide, Glycerine, Calciam cabonate, Perfume, Methylparaben

PURPOSE

Purpose: Skin protectant

WARNINGS

Warning:
Keep out of reach of children.
For external use only.
Avoid contact with eyes.
Do not swallow.

KEEP OUT OF REACH OF CHILDREN

INDICATIONS AND USAGE

Indication and usage:
Apply morning and evening on skin and spray in the skin slightly.
Suitable for all skin weakened or simply dehydrated.

DOSAGE AND ADMINISTRATION

Appiy the recommended amount to your face and spread smoothly outwards, patting as your spread.